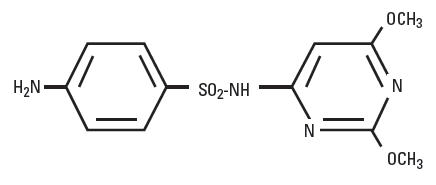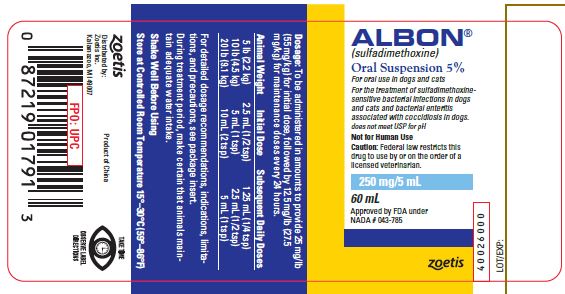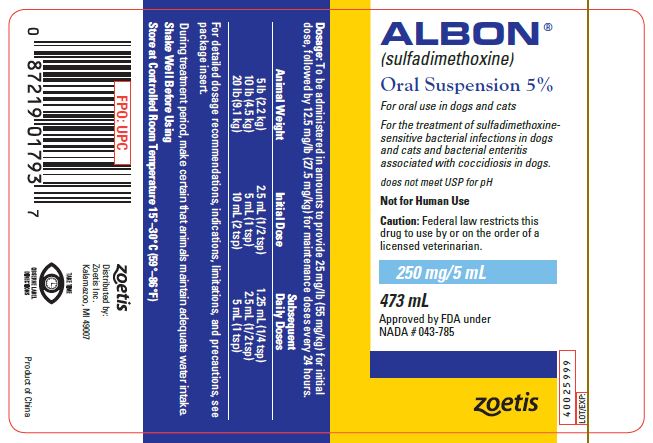 DRUG LABEL: Albon
NDC: 54771-8435 | Form: SUSPENSION
Manufacturer: Zoetis Inc.
Category: animal | Type: PRESCRIPTION ANIMAL DRUG LABEL
Date: 20191107

ACTIVE INGREDIENTS: SULFADIMETHOXINE 250 mg/5 mL

ALBON® (sulfadimethoxine)

ALBON

(sulfadimethoxine)

Oral Suspension 5%

VETERINARY INDICATIONS

For the treatment of sulfadimethoxine-sensitive bacterial infections in dogs and cats and bacterial enteritis associated with coccidiosis in dogs.

CAUTION

Federal law restricts this drug to use by or on the order of a licensed veterinarian.

DESCRIPTION

Albon is a low-dosage, rapidly absorbed, long-acting sulfonamide, effective for the treatment of a wide range of bacterial infections commonly encountered in dogs and cats.

Sulfadimethoxine is a white, almost tasteless and odorless compound. Chemically, it is N^1-(2,6-dimethoxy-4-pyrimidinyl) sulfanilamide. The structural formula is:

CLINICAL PHARMACOLOGY

Sulfadimethoxine has been demonstrated clinically or in the laboratory to be effective against a variety of organisms, such as streptococci, klebsiella, proteus, shigella, staphylococci, escherichia, and salmonella.^1,2 These organisms have been demonstrated in respiratory, genitourinary, enteric, and soft tissue infections of dogs and cats.

The systemic sulfonamides which include sulfadimethoxine are bacteriostatic agents. Sulfonamides competitively inhibit bacterial synthesis of folic acid (pteroylglutamic acid) from para-aminobenzoic acid. Mammalian cells are capable of utilizing folic acid in the presence of sulfonamides.

The tissue distribution of sulfadimethoxine, as with all sulfonamides, is a function of plasma levels, degree of plasma protein binding, and subsequent passive distribution in the tissues of the lipid-soluble un-ionized form. The relative amounts are determined by both its pKa and by the pH of each tissue. Therefore, levels tend to be higher in less acid tissue and body fluids or those diseased tissues having high concentrations of leucocytes.^2

In the dog, sulfadimethoxine is not acetylated as in most other animals, and it is excreted predominantly as the unchanged drug.^3 Sulfadimethoxine has a relatively high solubility at the pH normally occurring in the kidney, precluding the possibility of precipitation and crystalluria. Slow renal excretion results from a high degree of tubular reabsorption,^4 and plasma protein binding is very high, providing a blood reservoir of the drug. Thus, sulfadimethoxine maintains higher blood levels than most other long-acting sulfonamides. Single, comparatively low doses of Albon give rapid and sustained therapeutic blood levels.^1

To assure successful sulfonamide therapy (1) the drug must be given early in the course of the disease, and it must produce a high sulfonamide level in the body rapidly after administration, (2) therapeutically effective sulfonamide levels must be maintained in the body throughout the treatment period, (3) treatment should continue for a short period of time after the clinical signs have disappeared, and (4) the causative organisms must be sensitive to this class of drugs.

INDICATIONS AND USAGE

Albon is indicated for the treatment of respiratory, genitourinary tract, enteric, and soft tissue infections in dogs and cats:

- tonsillitis
- pharyngitis
- bronchitis
- pneumonia
- cystitis
- nephritis
- metritis
- pyometra

- pustular dermatitis
- anal gland infections
- abscesses
- wound infections
- bacterial enteritis
- canine salmonellosis
- bacterial enteritis associated with coccidiosis in dogs

when caused by streptococci, staphylococci, escherichia, salmonella, klebsiella, proteus or shigella organisms sensitive to sulfadimethoxine.

Limitations: Sulfadimethoxine is not effective in viral or rickettsial infections, and as with any antibacterial agent, occasional failures in therapy may occur due to resistant microorganisms. The usual precautions in sulfonamide therapy should be observed.

WARNING

Not for human use.

PRECAUTION

During treatment period, make certain that animals maintain adequate water intake.

If animals show no improvement within 2 or 3 days, reevaluate your diagnosis.

DOSAGE AND ADMINISTRATION:

Initial Dose: 25 mg/lb (55 mg/kg) of animal body weight.

Subsequent Daily Doses: 12.5 mg/lb (27.5 mg/kg) of animal body weight.

Dogs and cats should receive 1 teaspoonful of Albon Oral Suspension 5% per 10 lb of body weight (25 mg/lb or 55 mg/kg) as an initial dose, followed by 1/2 teaspoonful per 10 lb of body weight (12.5 mg/lb or 27.5 mg/kg) every 24 hours thereafter. Representative weights and doses are indicated in the following table:

Animal Weight | Initial Dose 25 mg/lb (55 mg/kg) | Subsequent Daily Doses 12.5 mg/lb (27.5 mg/kg)
5 lb (2.2 kg) | 1/2 tsp (2 1/2 mL) | 1/4 tsp (1 1/4 mL)
10 lb (4.5 kg) | 1 tsp (5 mL) | 1/2 tsp (2 1/2 mL)
20 lb (9.1 kg) | 2 tsp (10 mL) | 1 tsp (5 mL)
40 lb (18.2 kg) | 4 tsp (20 mL) | 2 tsp (10 mL)
80 lb (36.4 kg) | 8 tsp (40 mL) | 4 tsp (20 mL)

Treatment may be initiated with Albon Injection 40% to obtain effective blood levels almost immediately or to facilitate treatment of the fractious animal.

Length of treatment depends on the clinical response. In most cases treatment for 3–5 days is adequate. Treatment should be continued until the animal is asymptomatic for 48 hours.

TOXICITY AND SAFETY

Data regarding acute and chronic toxicities of sulfadimethoxine indicate the drug is very safe. The LD50 in mice is greater than 2 g/kg of body weight when administered intraperitoneally and greater than 16 g/kg when administered orally. In dogs receiving massive single oral doses of 3.2 g/kg of body weight, diarrhea was the only adverse effect observed. Dogs given 160 mg/kg of body weight orally daily for 13 weeks showed no signs of toxicity.

STORAGE

Store at controlled room temperature 15°–30°C (59°–86°F).

HOW SUPPLIED

Albon Oral Suspension is available in 60- and 473-mL bottles; each tsp (5 mL) contains 250 mg sulfadimethoxine in a custard-flavored carrier.

REFERENCES

1. Data on file, Zoetis Inc.

2. Stowe CM: The sulfonamides. In Jones LM (ed), Veterinary Pharmacology and Therapeutics, Ames, Iowa, Iowa State University Press, chapter 33, 1965.

3. Bridges JW, Kirby MR, Walker SR, et al: Species differences in the metabolism of sulfadimethoxine. Biochem J 109:851, 1968.

4. Baggot JD: Some aspects of drug persistence in domestic animals. Res Vet Sci 11(2):130, 1970.

Approved by FDA under NADA # 043-785
Product of China
zoetis
Distributed by:
Zoetis Inc.
Kalamazoo, MI 49007
40026001
Revised: January 2019